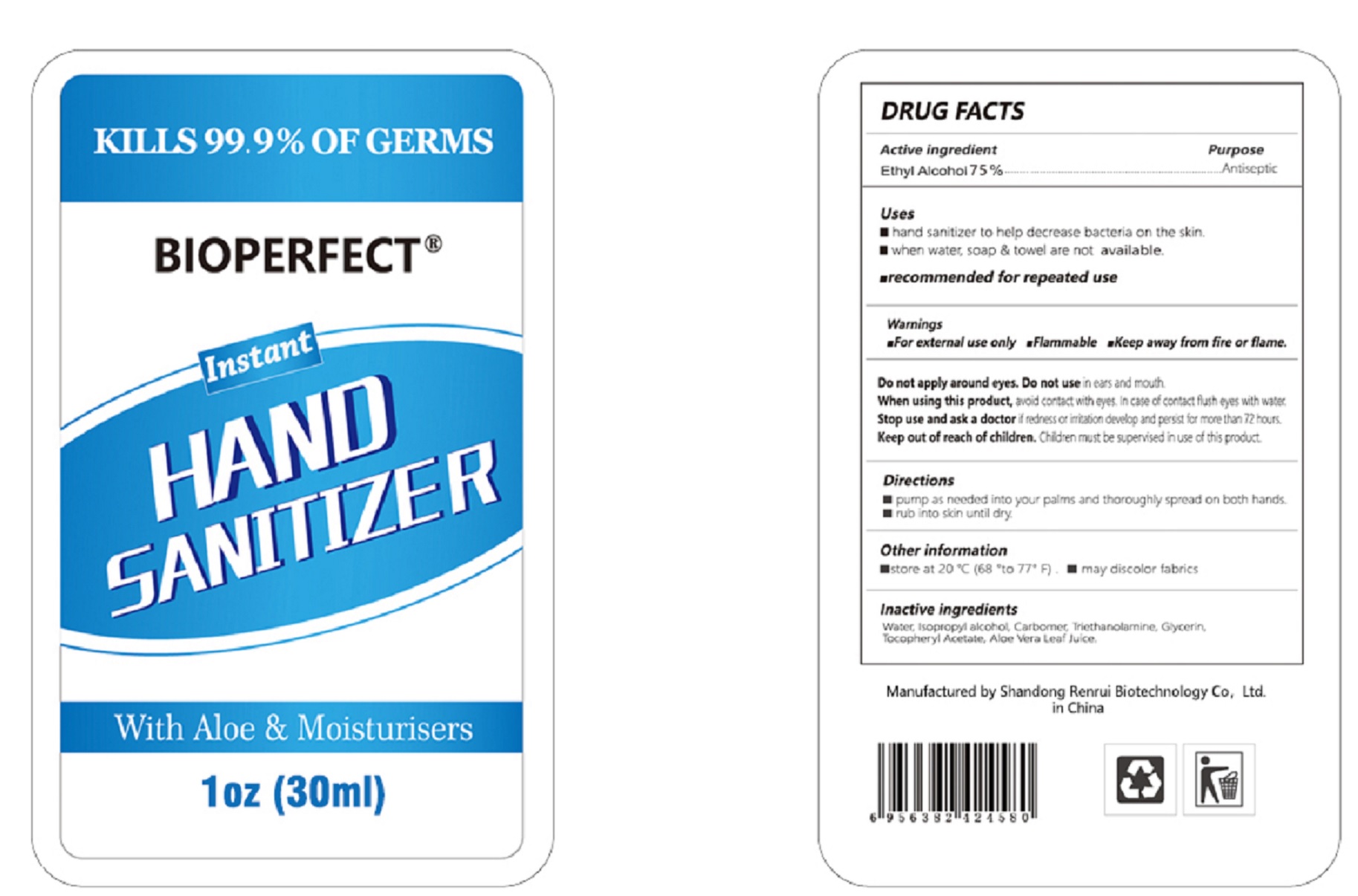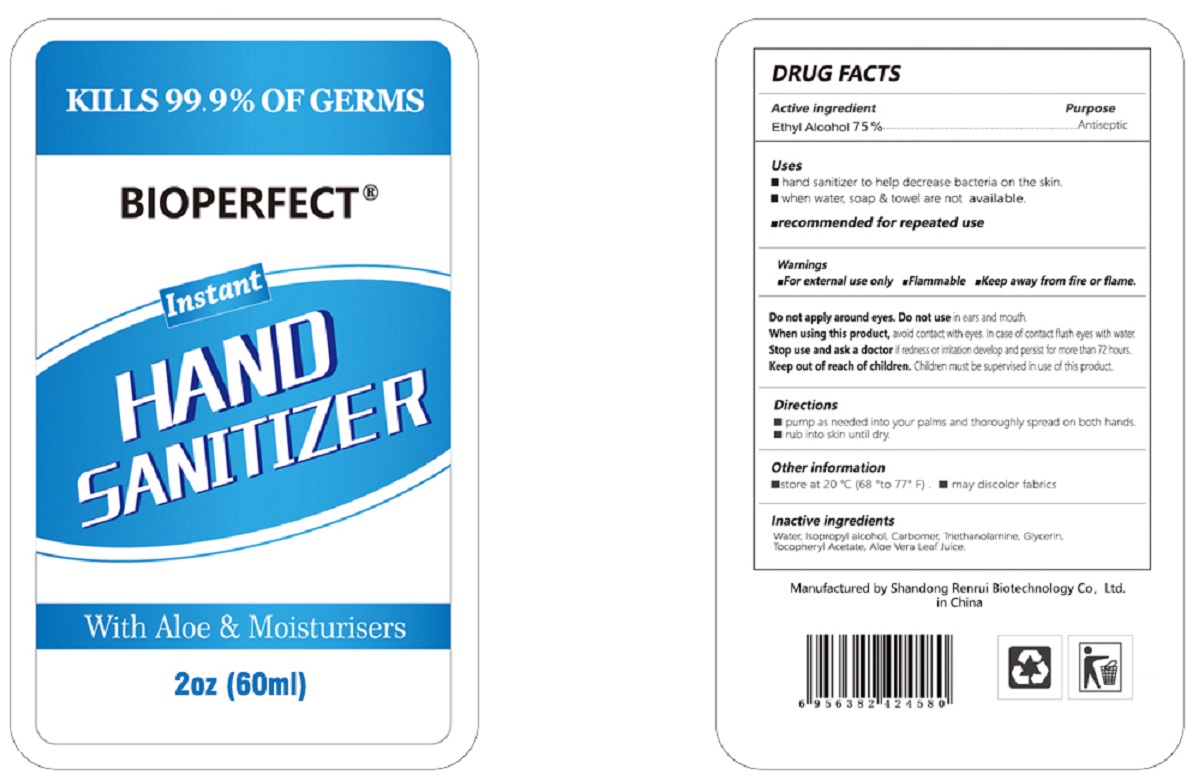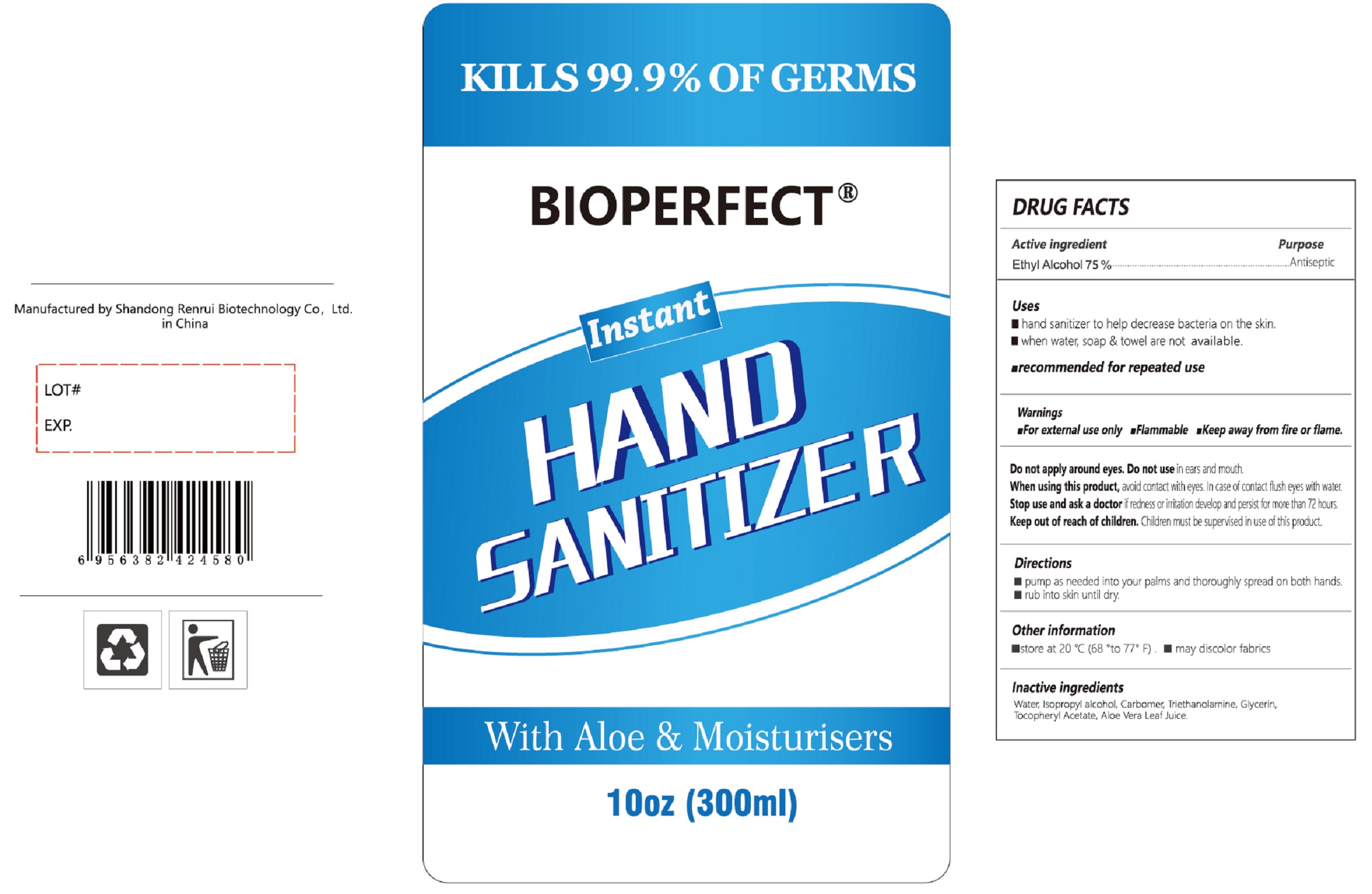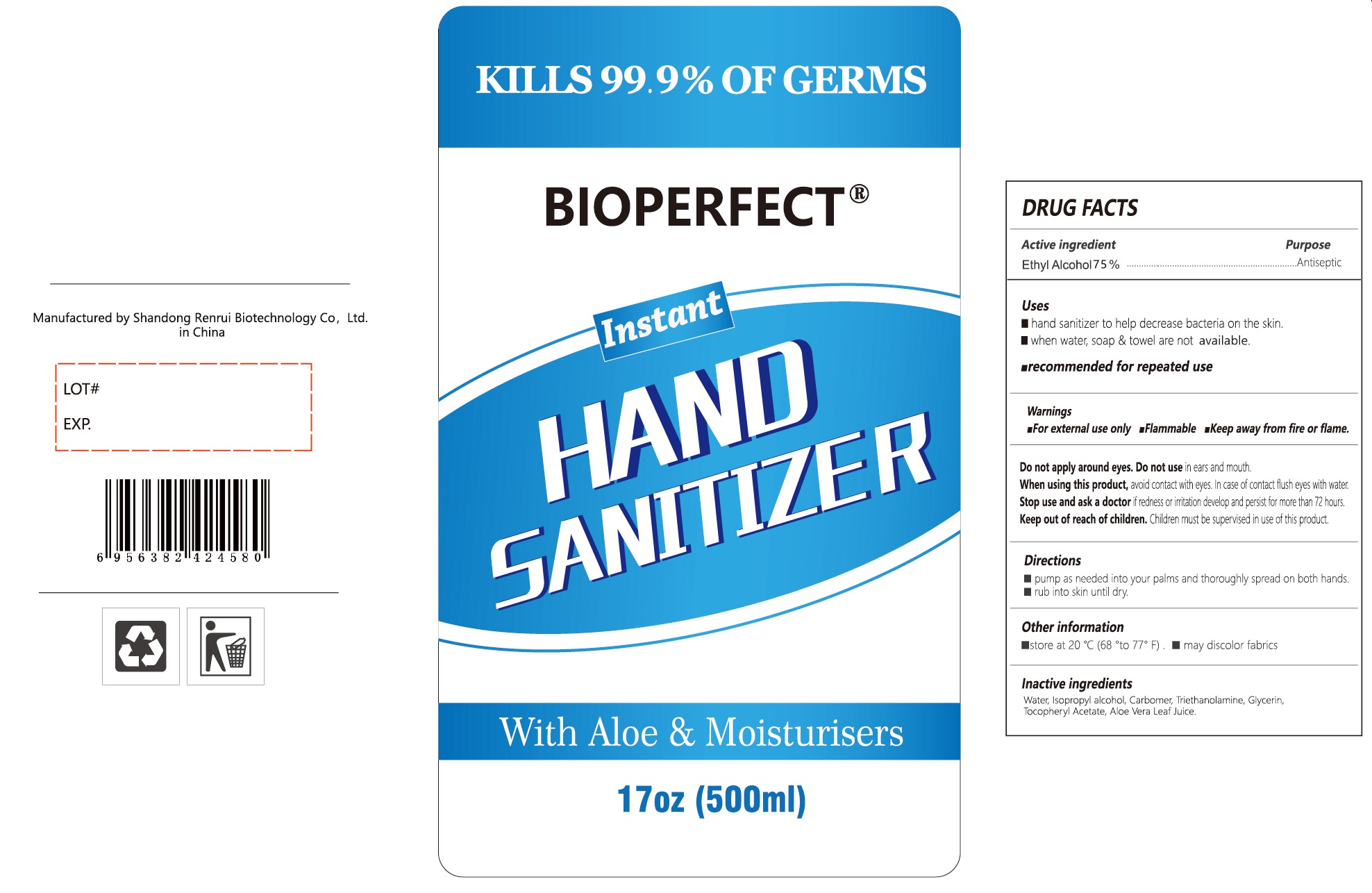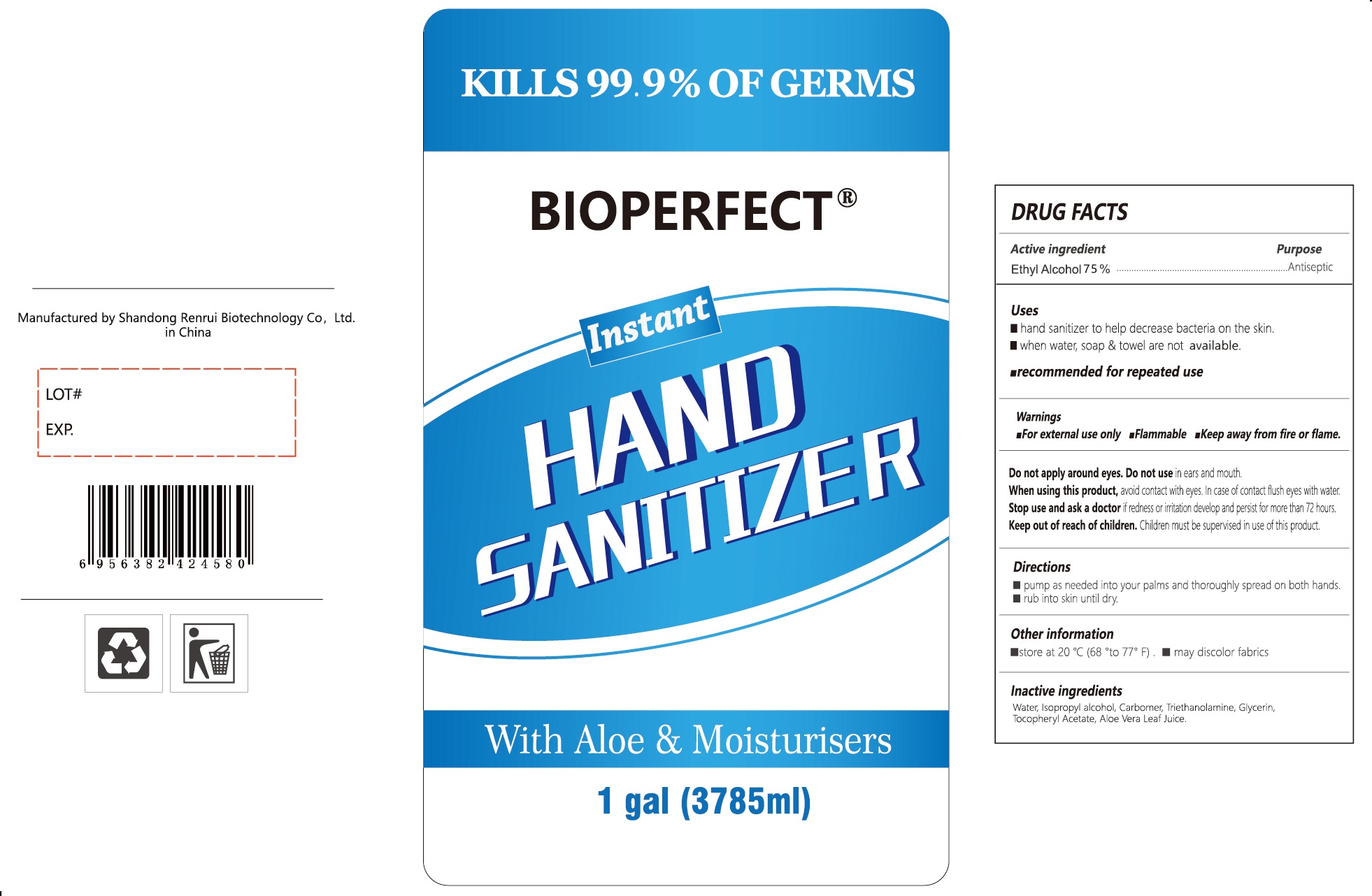 DRUG LABEL: BioPerfect Instant Hand Sanitizer
NDC: 77985-001 | Form: LIQUID
Manufacturer: Shandong Renrui Biotechnology Co, Ltd.
Category: otc | Type: HUMAN OTC DRUG LABEL
Date: 20200608

ACTIVE INGREDIENTS: ALCOHOL 0.75 mL/1 mL
INACTIVE INGREDIENTS: WATER; ISOPROPYL ALCOHOL; CARBOMER HOMOPOLYMER, UNSPECIFIED TYPE; TROLAMINE; GLYCERIN; .ALPHA.-TOCOPHEROL ACETATE; ALOE VERA LEAF

BioPerfect Instant Hand Sanitizer

Active ingredient

Ethyl Alcohol 75%

Purpose

Antiseptic

Uses

- hand sanitizer to help decrease bacteria on the skin.
- when water, soap & towel are not available.
- recommended for repeated use

Warnings

- For external use only
- Flamable
- Keep away from fire or flame.

Do not apply around eyes. Do not use

in ears and mouth.

When using this product,

avoid contact with eyes. In case of contact flush eyes with water.

Stop use and ask a doctor

if redness or irritation develop and persist for more than 72 hours.

Keep out of reach of children.

Children must be supervised in use of this product.

Directions

- pumps as needed into your palms and thoroughly spread on both hands.
- rub into skin until dry.

Other information

- store at 20 °C (68 °to 77° F)
- may discolor fabrics

Inacive ingredients

Water, Isopropyl alcohol, Carbomer, Triethanolamine, Glycerin, Tocopheryl Acetate, Aloe Vera Leaf Juice.